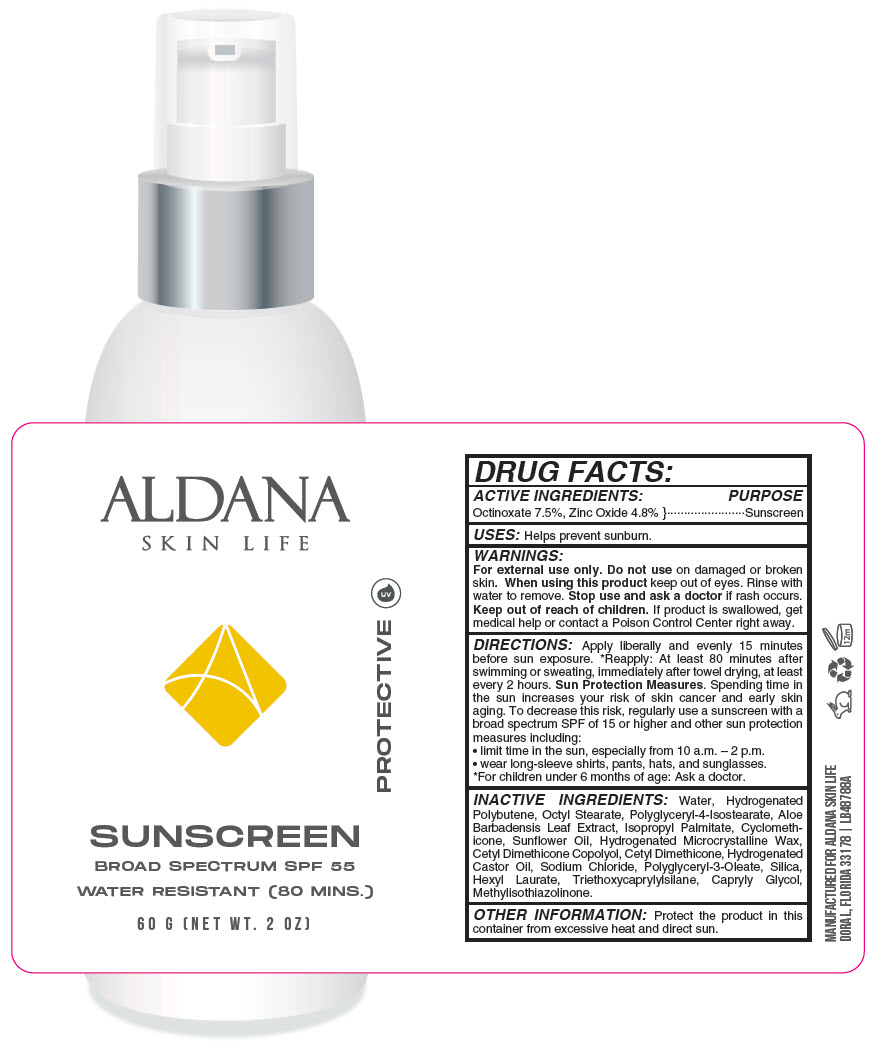 DRUG LABEL: Aldana Skin Life - Sunscreen Broad Spectrum SPF 55 Water Resistant (80 Mins.)
NDC: 66163-5500 | Form: LOTION
Manufacturer: Cosmetic Solutions LLC
Category: otc | Type: HUMAN OTC DRUG LABEL
Date: 20220412

ACTIVE INGREDIENTS: OCTINOXATE 75 mg/1 g; ZINC OXIDE 48 mg/1 g
INACTIVE INGREDIENTS: WATER; OCTYL STEARATE; POLYGLYCERYL-4 ISOSTEARATE; ALOE VERA LEAF; ISOPROPYL PALMITATE; CYCLOMETHICONE; SUNFLOWER OIL; HYDROGENATED CASTOR OIL; SODIUM CHLORIDE; POLYGLYCERYL-3 OLEATE; SILICON DIOXIDE; HEXYL LAURATE; TRIETHOXYCAPRYLYLSILANE; CAPRYLYL GLYCOL; METHYLISOTHIAZOLINONE

Aldana Skin Life - Sunscreen Broad Spectrum SPF 55 Water Resistant (80 Mins.)

DRUG FACTS:

ACTIVE INGREDIENTS

Octinoxate 7.5%, Zinc Oxide 4.8%

PURPOSE

Sunscreen

USES

Helps prevent sunburn.

WARNINGS

For external use only. Do not use on damaged or broken skin. When using this product keep out of eyes. Rinse with water to remove. Stop use and ask a doctor if rash occurs.

Keep out of reach of children. If product is swallowed, get medical help or contact a Poison Control Center right away.

DIRECTIONS

Apply liberally and evenly 15 minutes before sun exposure. [For children under 6 months of age: Ask a doctor.] Reapply: At least 80 minutes after swimming or sweating, immediately after towel drying, at least every 2 hours. Sun Protection Measures. Spending time in the sun increases your risk of skin cancer and early skin aging. To decrease this risk, regularly use a sunscreen with a broad spectrum SPF of 15 or higher and other sun protection measures including:

- limit time in the sun, especially from 10 a.m. – 2 p.m.
- wear long-sleeve shirts, pants, hats, and sunglasses.

INACTIVE INGREDIENTS

Water, Hydrogenated Polybutene, Octyl Stearate, Polyglyceryl-4-Isostearate, Aloe Barbadensis Leaf Extract, Isopropyl Palmitate, Cyclomethicone, Sunflower Oil, Hydrogenated Microcrystalline Wax, Cetyl Dimethicone Copolyol, Cetyl Dimethicone, Hydrogenated Castor Oil, Sodium Chloride, Polyglyceryl-3-Oleate, Silica, Hexyl Laurate, Triethoxycaprylylsilane, Capryly Glycol, Methylisothiazolinone.

OTHER INFORMATION

Protect the product in this container from excessive heat and direct sun.

PRINCIPAL DISPLAY PANEL - 60 G Bottle Label

ALDANA
SKIN LIFE

uv
PROTECTIVE

SUNSCREEN

BROAD SPECTRUM SPF 55

WATER RESISTANT (80 MINS.)

60 G (NET WT. 2 OZ)